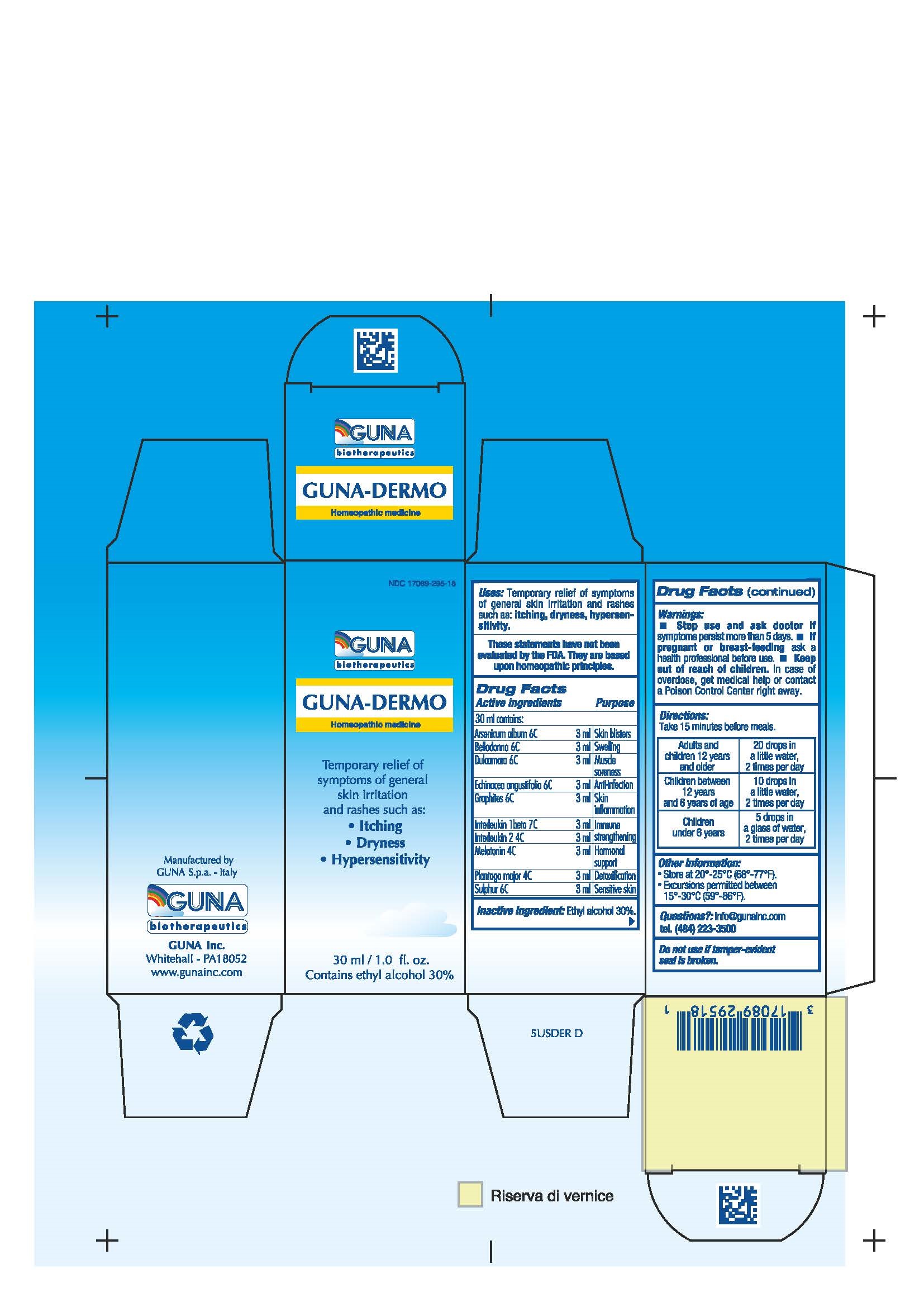 DRUG LABEL: GUNA-DERMO
NDC: 17089-295 | Form: SOLUTION/ DROPS
Manufacturer: Guna spa
Category: homeopathic | Type: HUMAN OTC DRUG LABEL
Date: 20181221

ACTIVE INGREDIENTS: ALDESLEUKIN 4 [hp_C]/30 mL; ARSENIC TRIOXIDE 6 [hp_C]/30 mL; ATROPA BELLADONNA 6 [hp_C]/30 mL; CANAKINUMAB 7 [hp_C]/30 mL; ECHINACEA ANGUSTIFOLIA 6 [hp_C]/30 mL; GRAPHITE 6 [hp_C]/30 mL; MELATONIN 4 [hp_C]/30 mL; PLANTAGO MAJOR 4 [hp_C]/30 mL; SOLANUM DULCAMARA FLOWER 6 [hp_C]/30 mL; SULFUR 6 [hp_C]/30 mL
INACTIVE INGREDIENTS: ALCOHOL 9 mL/30 mL

GUNA-DERMO

ACTIVE INGREDIENTS/PURPOSE

ARSENICUM ALBUM 6C SKIN BLISTERS
BELLADONNA 6C SWELLING
DULCAMARA 6C MUSCLE SORENESS
ECHINACEA ANGUSTIFOLIA 6C ANTI-INFECTION
GRAPHITES 6C SKIN INFLAMMATION
INTERLEUKIN 1 BETA 7C IMMUNE STRENGTHENING
INTERLEUKIN 2 4C IMMUNE STRENGTHENING
MELATONIN 4C HORMONAL SUPPORT
PLANTAGO MAJOR 4C DETOXIFICATION
SULPHUR 6C SENSITIVE SKIN

USES

Temporary relief of symptoms of general skin irritation and rashes such as:

- Itching
- Dryness
- Hypersensitivity

WARNINGS

Stop use and ask doctor if symptoms persist more than 5 days.
If pregnant or breast-feeding ask a health professional before use.
Keep out of reach of children. In case of overdose, get medical help or contact a Poison Control Center right away.
Contains ethyl alcohol 30%

PREGNANCY

If pregnant or breast-feeding ask a doctor before use

WARNINGS

Keep this and all medicines out of reach of children

DIRECTIONS

Adults and children 12 years and older 20 drops in a little water, 2 times per day
Children between 12 years and 6 years of age 10 drops in a little water, 2 times per day
Children under 6 years 5 drops in a glass of water, 2 times per day

QUESTIONS

Questions?: info@gunainc.com, tel. (484) 223-3500

INDICATIONS AND USAGE

Take 15 minutes before meals

Inactive ingredient. Ethyl alcohol 30%.